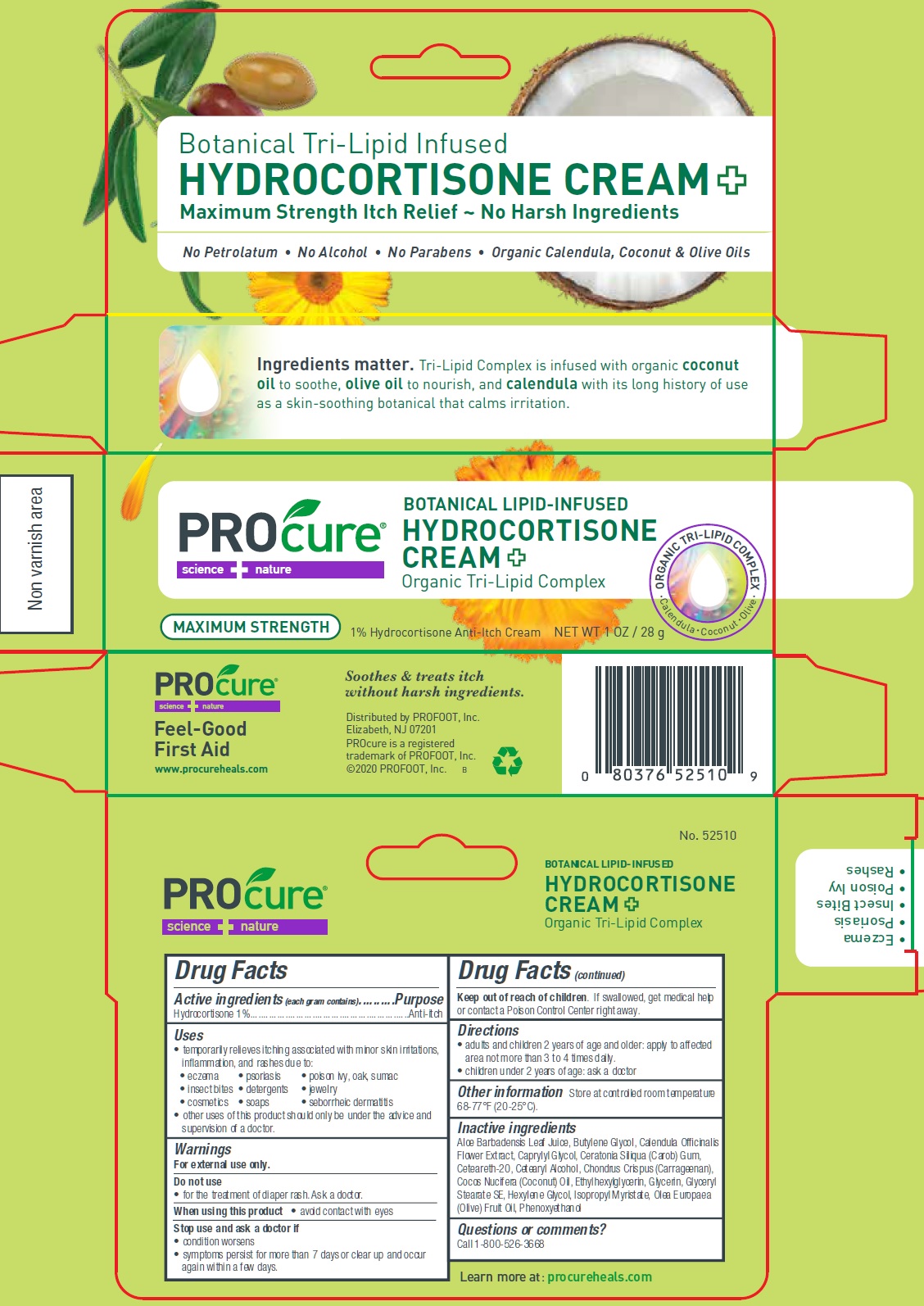 DRUG LABEL: ProCure Hydrocortisone Cream Plus
NDC: 29784-142 | Form: CREAM
Manufacturer: Rooftop Consumer Health, Inc.
Category: otc | Type: HUMAN OTC DRUG LABEL
Date: 20260129

ACTIVE INGREDIENTS: HYDROCORTISONE 10 mg/1 g
INACTIVE INGREDIENTS: ALOE VERA LEAF; BUTYLENE GLYCOL; CALENDULA OFFICINALIS FLOWER; CAPRYLYL GLYCOL; LOCUST BEAN GUM; POLYOXYL 20 CETOSTEARYL ETHER; CETOSTEARYL ALCOHOL; CHONDRUS CRISPUS CARRAGEENAN; COCONUT OIL; ETHYLHEXYLGLYCERIN; GLYCERIN; GLYCERYL STEARATE SE; HEXYLENE GLYCOL; ISOPROPYL MYRISTATE; OLIVE OIL; PHENOXYETHANOL

ProCure Hydrocortisone Cream Plus

Active ingredients (each gram contains)

Hydrocortisone 1%

Purpose

Anti-itch

Uses

• temporarily relieves itching associated with minor skin irritations, inflammation, and rashes due to: • eczema • psoriasis • poison ivy, oak, sumac • insect bites • detergents • jewelry • cosmetics • soaps • seborrheic dermatitis • other uses of this product should only be under the advice and supervision of a doctor.

Warnings

For external use only.

Do not use

• for the treatment of diaper rash. Ask a doctor.

When using this product

• avoid contact with eyes

Stop use and ask a doctor if

• condition worsens • symptoms persist for more than 7 days or clear up and occur again within a few days.

Keep out of reach of children

If swallowed, get medical help or contact a Poison Control Center right away.

Directions

• adults and children 2 years of age and older: apply to affected area not more than 3 to 4 times daily. • children under 2 years of age: ask a doctor

Other information

Store at controlled room temperature 68-77°F (20-25°C).

Inactive ingredients

Aloe Barbadensis Leaf Juice, Butylene Glycol, Calendula Officinalis Flower Extract, Caprylyl Glycol, Ceratonia Siliqua (Carob) Gum, Ceteareth-20, Cetearyl Alcohol, Chondrus Crispus (Carrageenan), Cocos Nucifera (Coconut) Oil, Ethylhexylglycerin, Glycerin, Glyceryl Stearate SE, Hexylene Glycol, Isopropyl Myristate, Olea Europaea (Olive) Fruit Oil, Phenoxyethanol

Questions or comments?

Call 1-800-526-3668